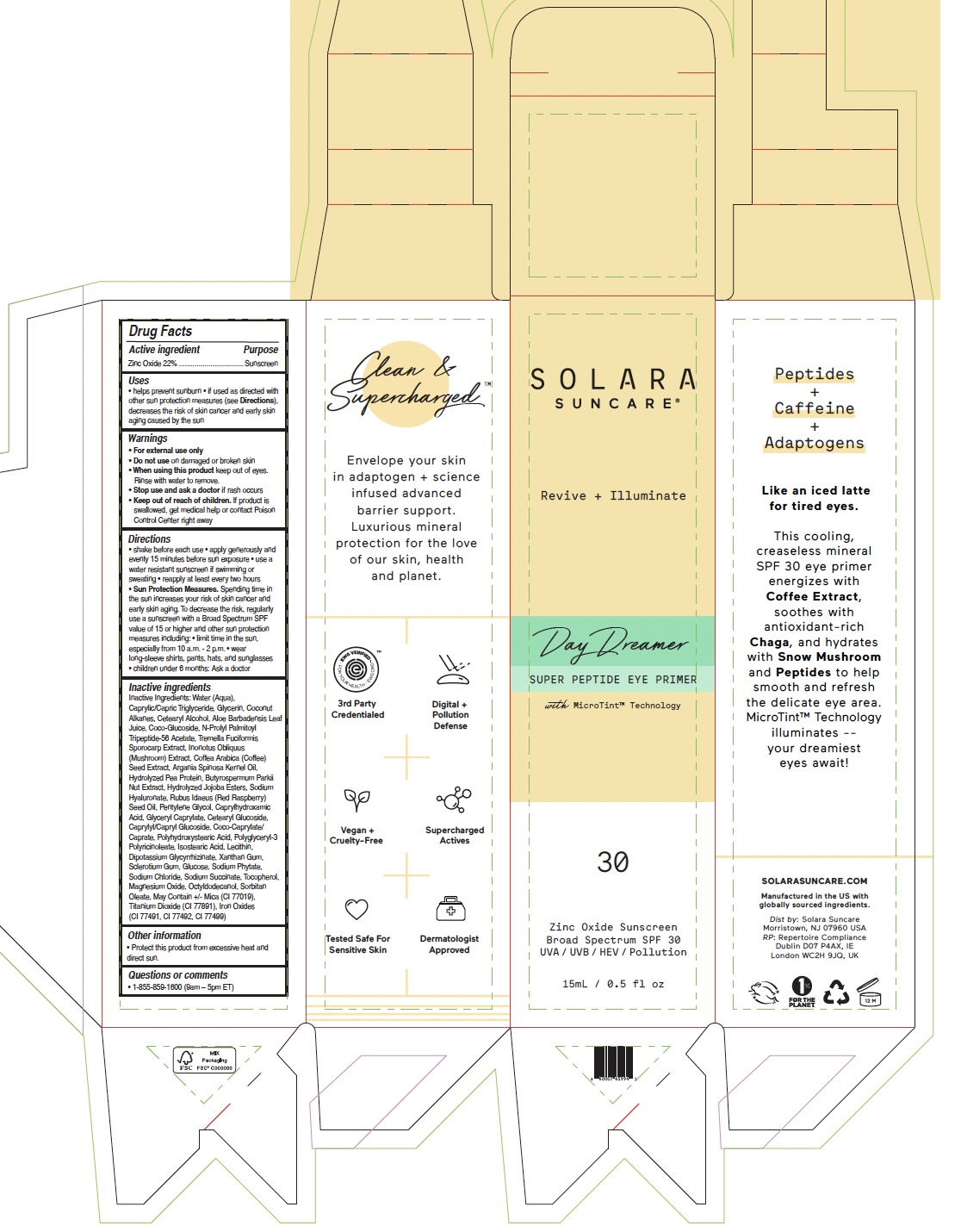 DRUG LABEL: SOLARA SUNCARE - DAY DREAMER
NDC: 73054-128 | Form: LOTION
Manufacturer: SOLARA SUNCARE, INC.
Category: otc | Type: HUMAN OTC DRUG LABEL
Date: 20250815

ACTIVE INGREDIENTS: ZINC OXIDE 22 g/100 mL
INACTIVE INGREDIENTS: TOCOPHEROL; HYDROLYZED JOJOBA ESTERS; CETEARYL ALCOHOL; ALOE BARBADENSIS LEAF JUICE; PENTYLENE GLYCOL; CETEARYL GLUCOSIDE; LECITHIN, SUNFLOWER; SODIUM CHLORIDE; OCTYLDODECANOL; ARGANIA SPINOSA KERNEL OIL; CI 77492; CI 77499; COCO-CAPRYLATE/CAPRATE; SODIUM PHYTATE; SODIUM SUCCINATE; MICA; INONOTUS OBLIQUUS FRUITING BODY; SORBITAN OLEATE; COFFEA ARABICA (COFFEE) SEED OIL; COCO-GLUCOSIDE; COCONUT ALKANES; RUBUS IDAEUS (RASPBERRY) SEED OIL; SODIUM HYALURONATE; GLYCERYL CAPRYLATE; TREMELLA FUCIFORMIS FRUITING BODY; BUTYROSPERMUM PARKII (SHEA) BUTTER; MAGNESIUM OXIDE; CI 77891; CI 77491; POLYGLYCERYL-3 PENTARICINOLEATE; CAPRYLIC/CAPRIC TRIGLYCERIDE; GLUCOSE; XANTHAN GUM; SCLEROTIUM GUM; DIPOTASSIUM GLYCYRRHIZATE; N-PROLYL PALMITOYL TRIPEPTIDE-56 ACETATE; CAPRYLYL/CAPRYL GLUCOSIDE; POLYHYDROXYSTEARIC ACID (2300 MW); ISOSTEARIC ACID; WATER; GLYCERIN; CAPRYLHYDROXAMIC ACID; PEA PROTEIN

SOLARA (as PLD) - Day Dreamer - eye cream

ACTIVE INGREDIENT

Zinc Oxide 22%

PURPOSE

Sunscreen

USES

- helps prevent sunburn
- if used as directed with other sun protection measures (see Directions), decreases the risk of skin cancer and early skin aging caused by the sun

Warnings

For external use only

Do not use on damaged or broken skin

When using this product keep out of eyes. Rinse with water to remove.

Stop use and ask a doctor if rash occurs

Keep out of reach of children. If product is swallowed, get medical help or contact Poison Control Center right away.

DIRECTIONS

- shake or knead before each use
- apply generously and evenly 15 minutes before sun exposure
- use a water resistant sunscreen if swimming or sweating
- reapply at least every two hours

- Sun Protection Measures. Spending time in the sun increases your risk of skin cancer and early skin aging. To decrease the risk, regularly use asunscreen with a Broad Spectrum SPF value of 15 or higher and other sun protection measures including:
- limit time in the sun, especially from 10 a.m. - 2 p.m.
- wear long-sleeve shirts, pants, hats, and sunglasses
- children under 6 months: Ask a doctor

INACTIVE INGREDIENTS

Water (Aqua), Caprylic/Capric Triglyceride, Glycerin, Coconut Alkanes, Cetearyl Alcohol, Aloe Barbadensis Leaf Juice, Coco Glucoside, N-Prolyl Palmitoyl Tripeptide-56 Acetate, Tremella Fuciformis Sporocarp Extract, Inonotus Obliquus (Mushroom) Extract, Coffea Arabica (Coffee) Seed Extract, Argania Spinosa Kernel Oil, Hydrolyzed Pea Protein, Butyrospermum Parkii Nut Extract, Hydrolyzed Jojoba Esters, Sodium Hyaluronate, Rubus Idaeus (Red Raspberry) Seed Oil, Pentylene Glycol, Caprylhydroxamic Acid, Glyceryl Caprylate, Cetearyl Glucoside, Caprylyl/Capryl Glucoside, Coco-Caprylate/ Caprate, Polyhydroxystearic Acid, Polyglyceryl-3 Polyricinoleate, Isostearic Acid, Lecithin, Dipotassium Glycyrrhizinate, Xanthan Gum, Sclerotium Gum, Glucose, Sodium Phytate, Sodium Chloride, Sodium Succinate, Tocopherol, Magnesium Oxide, Octyldodecanol, Sorbitan Oleate, May Contain +/- Mica (CI 77019), Titanium Dioxide (CI 77891), Iron Oxides (CI 77491, CI 77492, CI 77499)

OTHER INFORMATION

- Protect this product from excessive heat and direct sun.

QUESTIONS OR COMMENTS

- 1-855-859-1600 (9am – 5pm ET)